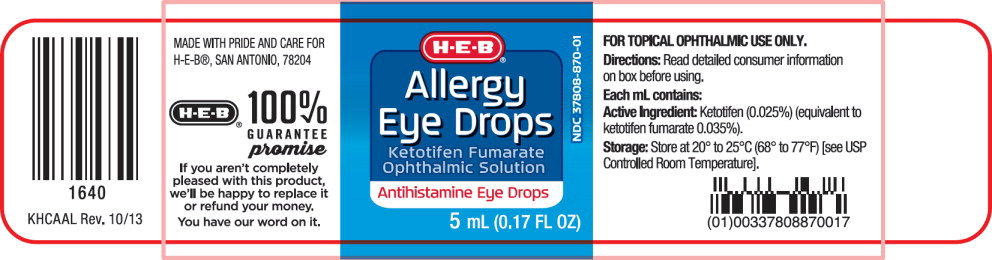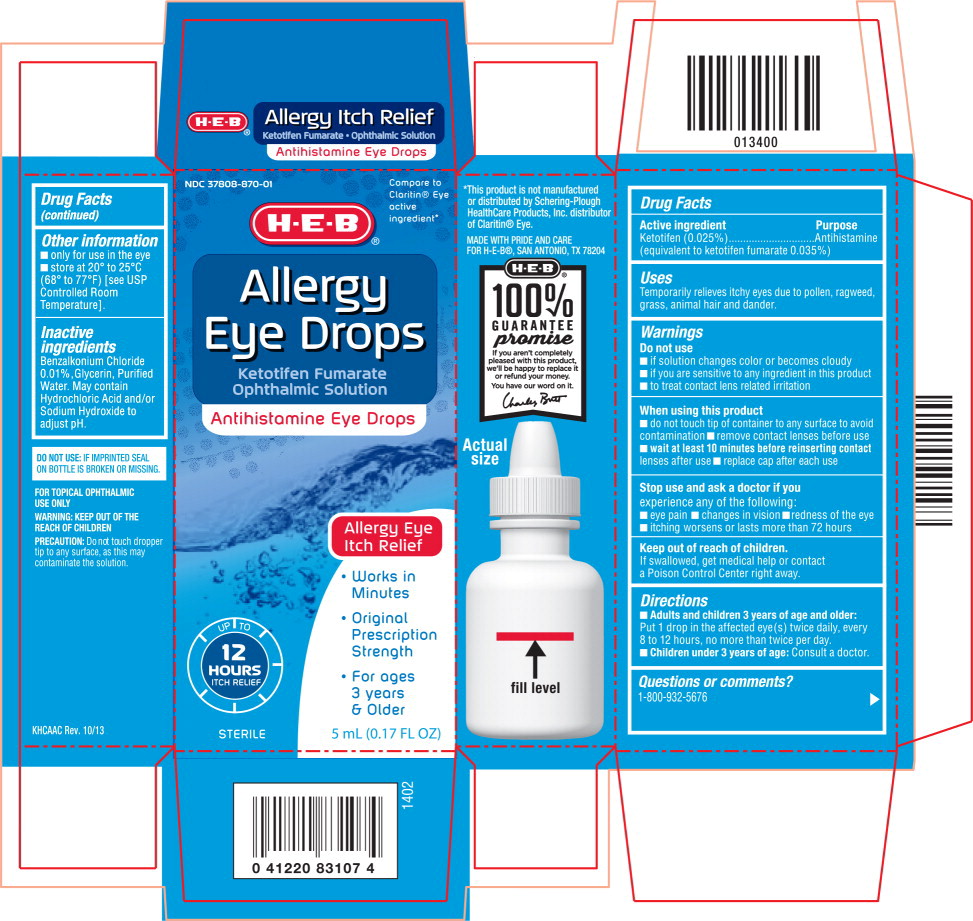 DRUG LABEL: Allergy Eye Drops
NDC: 37808-870 | Form: SOLUTION/ DROPS
Manufacturer: H E B
Category: otc | Type: HUMAN OTC DRUG LABEL
Date: 20220125

ACTIVE INGREDIENTS: Ketotifen Fumarate 0.35 mg/1 mL
INACTIVE INGREDIENTS: Benzalkonium Chloride; Glycerin; Water; Hydrochloric Acid; Sodium Hydroxide

Drug Facts

Active ingredient

Ketotifen (0.025%)

(equivalent to ketotifen fumarate 0.035%)

Purpose

Antihistamine

Uses

Temporarily relieves itchy eyes due to pollen, ragweed, grass, animal hair and dander.

Warnings

Do not use

- if solution changes color or becomes cloudy
- if you are sensitive to any ingredient in this product
- to treat contact lens related irritation

When using this product

- do not touch tip of container to any surface to avoid contamination
- remove contact lenses before use
- wait at least 10 minutes before reinserting contact lenses after use
- replace cap after each use

Stop use and ask a doctor if you experience any of the following:

- eye pain
- changes in vision
- redness of the eye
- itching worsens or lasts more than 72 hours

Keep out of reach of children.

If swallowed, get medical help or contact a Poison Control Center right away.

Directions

- Adults and children 3 years of age and older: Put 1 drop in the affected eye(s) twice daily, every 8 to 12 hours, no more than twice per day.
- Children under 3 years of age: Consult a doctor.

Other information

- only for use in the eye
- store at 20° to 25°C (68° to 77°F) [see USP Controlled Room Temperature].

Inactive ingredients

Benzalkonium Chloride 0.01%, Glycerin, Purified Water. May contain Hydrochloric Acid and/or Sodium Hydroxide to adjust pH.

Questions or comments?

1-800-932-5676

Principal Display Panel Text for Container Label:

H ■ E ■ B Logo®

NDC 37808-870-01

Allergy

Eye Drops

Ketotifen Fumarate

Ophthalmic Solution

Antihistamine Eye Drops

5 mL (0.17 FL OZ)

Principal Display Panel Text for Carton Label:

NDC 37808-870-01 Compare to

Claritin® Eye

active

ingredient*

H ■ E ■ B Logo®

Allergy

Eye Drops

Ketotifen Fumarate

Ophthalmic Solution

Antihistamine Eye Drops

Allergy Eye

Itch Relief

• Works in

Minutes

• Original

Prescription

Strength

• For ages

3 years

& Older

UP TO

12

HOURS

ITCH RELIEF

STERILE 5 mL (0.17 FL OZ)